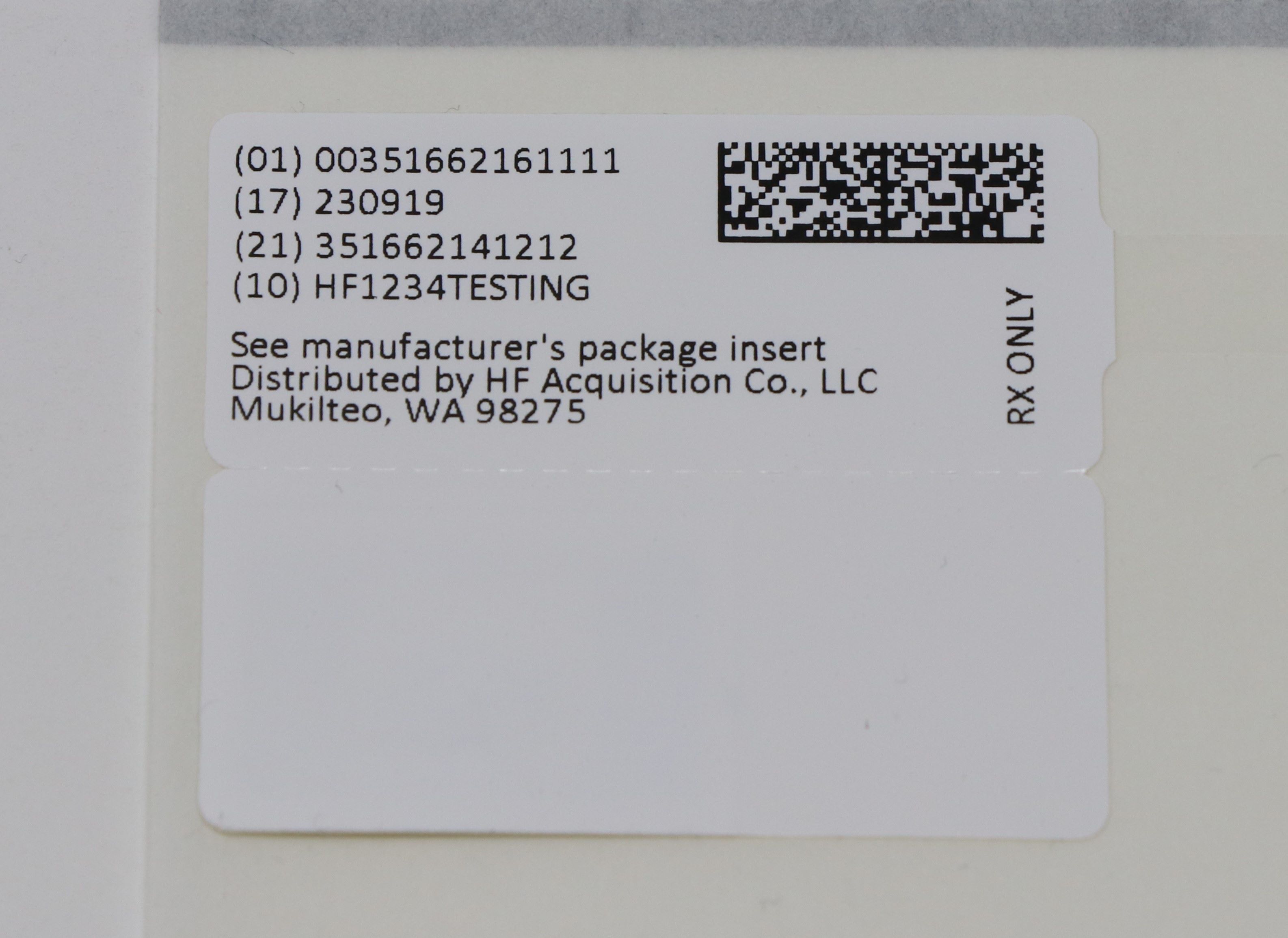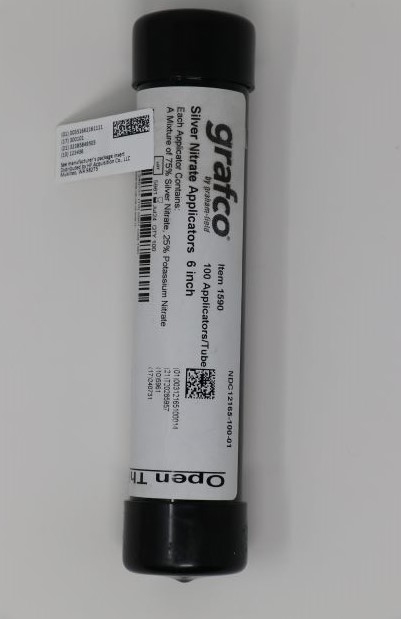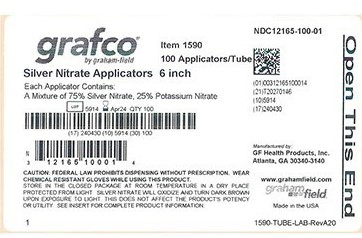 DRUG LABEL: GRAFCO SILVER NITRATE (75% SILVER NITRATE, 25% POTASSIUM NITRATE)
NDC: 51662-1611 | Form: STICK
Manufacturer: HF Acquisition Co LLC, DBA HealthFirst
Category: prescription | Type: HUMAN PRESCRIPTION DRUG LABEL
Date: 20240325

ACTIVE INGREDIENTS: POTASSIUM NITRATE 12.74 mg/1 1; SILVER NITRATE 38.21 mg/1 1
INACTIVE INGREDIENTS: HYDROCHLORIC ACID 0.036 mg/1 1; SODIUM CHLORIDE 0.0153 mg/1 1

GRAFCO SILVER NITRATE 6" APPLICATORS (75% SILVER NITRATE, 25% POTASSIUM NITRATE) 100 PER TUBE

INDICATIONS & USAGE

INDICATIONS: For cauterization of skin or mucous membrane and for removing warts and granulated tissue.

DOSAGE & ADMINISTRATION

Moisten the applicator tip with distilled, deionized or purified water and apply the silver nitrate to the affected area by holding, rubbing, or rotating the tip along the affected tissue. The strength of the action is controlled by the dilution with distilled, deionized or purified water. One silver nitrate applicator is generally sufficient for each application. The action of the silver nitrate can be stopped by washing the area with saline solution (0.9% sodium chloride). Using saline solution to wet the applicator tips, or residual saline from wound flushing/washing will interfere with the action of silver nitrate resulting in cauterization failure. Only use distilled, deionized or purified water to wet applicator tips. Blot dry wounds that have been flushed/washed with saline prior to applying silver nitrate.

CONTRAINDICATIONS

Silver salts stain tissue black due to deposition of reduced silver. The stain gradually disappears within a period of two weeks. Prolonged ingestion or absorption of silver compounds leads to deposition of silver in connective tissues, producing a slate-blue discoloration of the skin known as argyria. This discoloration may also appear on mucous membranes such as the margins of gums. The sclera of the eye is also stained.

WARNINGS & PRECAUTIONS

WARNING: KEEP OUT OF REACH OF CHILDREN. The active ingredients are poisonous and may be fatal when ingested in sufficient doses. The symptoms include toxic gastroenteritis, which may lead to coma, convulsion, paralysis and profound alteration of respiration. If poisoning occurs, immediately consult a physician.
WARNING: DO NOT USE ON THE EYES. In case of eye contact, hold eyes open and immediately flush thoroughly with water for at least 15 minutes and consult a physician.
CAUTION: SILVER NITRATE IS A CAUSTIC SUBSTANCE. Chemical burns may result from inappropriate use of product.
• Wear chemical resistant gloves while using this product. Wear other appropriate personal protective equipment as needed.
• Take care to confine the silver nitrate to the area being treated by using an appropriate physical or chemical barrier to prevent staining or burning of untreated tissue.
• Skin contact time with applicators should be minimal when used on thin delicate skin or neonates.
• Avoid prolonged contact with skin or other surfaces since staining may occur.
CAUTION: FEDERAL LAW PROHIBITS DISPENSING WITHOUT PRESCRIPTION.

STORAGE

Store in the closed package at room temperature in a dry place protected from light. Silver nitrate will oxidize and turn dark brown upon exposure to light, however this does not affect the product’s potency or utility. Exposure to moisture can cause the tip to break or loosen from the applicator. Store away from vaporous chemicals.

DISPOSAL

Expired or unused applicators may be returned for disposal to: GF Health Products, Inc., 33 Plan Way, Bldg. # 2, Warwick, RI 02886, or disposed of according to applicable federal, state and local regulations.

HOW SUPPLIED

NDC 51662-1611-1

GRAFCO SILVER NITRATE 6" APPLICATORS (75% SILVER NITRATE, 25% POTASSIUM NITRATE) 100 PER TUBE

HF Acquisition Co LLC, DBA HealthFirst
11629 49th Pl W.

Mukilteo, WA 98275

PRINCIPAL DISPLAY PANEL - NDC 51662-1611-1

51662-1611-1 Serialized Tube Labeling

Tube Labeling